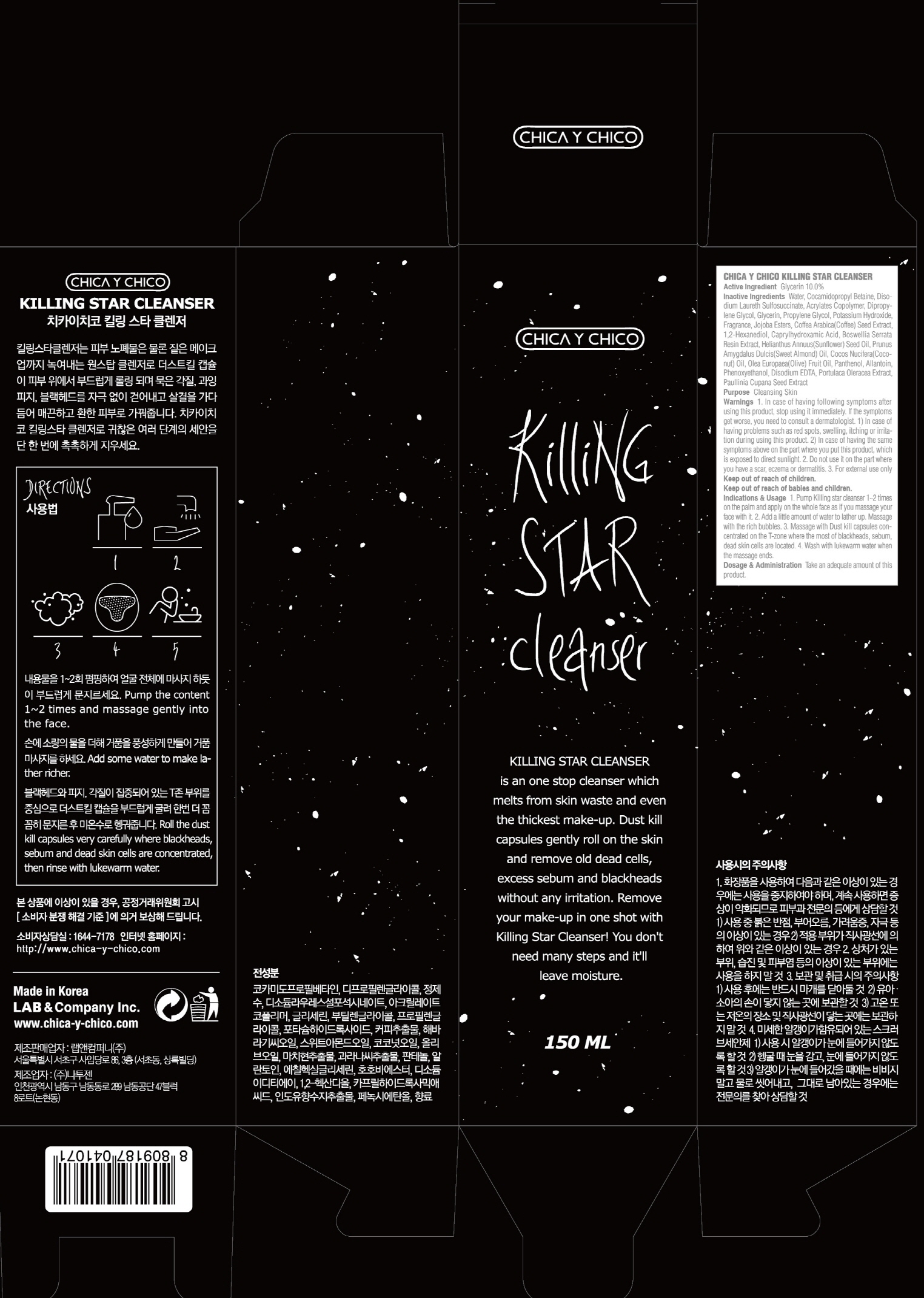 DRUG LABEL: CHICA Y CHICO Killing Star Cleanser
NDC: 69457-040 | Form: GEL
Manufacturer: LAB & Company Inc.
Category: otc | Type: HUMAN OTC DRUG LABEL
Date: 20160803

ACTIVE INGREDIENTS: Glycerin 15.0 g/150 mL
INACTIVE INGREDIENTS: Water; Cocamidopropyl Betaine

ACTIVE INGREDIENT

Active Ingredient: Glycerin 10.0%

INACTIVE INGREDIENT

Inactive Ingredients: Water, Cocamidopropyl Betaine, Disodium Laureth Sulfosuccinate, Acrylates Copolymer, Dipropylene Glycol, Glycerin, Propylene Glycol, Potassium Hydroxide, Fragrance, Jojoba Esters, Coffea Arabica(Coffee) Seed Extract, 1,2-Hexanediol, Caprylhydroxamic Acid, Boswellia Serrata Resin Extract, Helianthus Annuus(Sunflower) Seed Oil, Prunus Amygdalus Dulcis(Sweet Almond) Oil, Cocos Nucifera(Coconut) Oil, Olea Europaea(Olive) Fruit Oil, Panthenol, Allantoin, Phenoxyethanol, Disodium EDTA, Portulaca Oleracea Extract, Paullinia Cupana Seed Extract

PURPOSE

Purpose: Cleansing Skin

WARNINGS

Warnings: 1. In case of having following symptoms after using this product, stop using it immediately. If the symptoms get worse, you need to consult a dermatologist. 1) In case of having problems such as red spots, swelling, itching or irritation during using this product, 2) In case of having the same symptoms above on the part where you put this product, which is exposed to direct sunlight. 2. Do not use it on the part where you have a scar, eczema or dermatitis. 3. For external use only

Keep out of reach of children: Keep out of reach of babies and children.

INDICATIONS & USAGE

Indications & Usage: 1. Pump Killing star cleanser 1~2 times on the palm and apply on the whole face as if you massage your face with it. 2. Add a little amount of water to lather up. Massage with the rich bubbles. 3. Massage with Dust kill capsules concentrated on the T-zone where the most of blackheads, sebum, dead skin cells are located. 4. Wash with lukewarm water when the massage ends.

DOSAGE & ADMINISTRATION

Dosage & Administration: Take an adequate amount of this product.